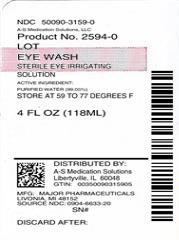 DRUG LABEL: Eye Wash
NDC: 50090-3159 | Form: SOLUTION
Manufacturer: A-S Medication Solutions
Category: otc | Type: HUMAN OTC DRUG LABEL
Date: 20200218

ACTIVE INGREDIENTS: WATER 99.05 mL/100 mL
INACTIVE INGREDIENTS: BORIC ACID; SODIUM BORATE; SODIUM CHLORIDE; HYDROCHLORIC ACID; EDETATE DISODIUM; POLIHEXANIDE

Major Eye Wash

Active ingredient

Purified water (99.05%)

Purpose

Eyewash

Uses

washes the eye to help relieve

- irritation
- stinging
- discomfort
- itching

by removing

- loose foreign material
- air pollutants (smog or pollen)
- chlorinated water

Warnings

For external use only

Do not use

- if solution changes color or becomes cloudy

When using this product

- remove contact lenses before using
- do not touch tip of container to any surface to avoid contamination
- replace cap after use

Stop use and ask a doctor if

- you experience eye pain, changes in vision, continued redness or irritation of the eye
- condition worsens or persists
- you have open wounds in or near the eye. Get medical help right away.

Keep out of reach of children.

If swallowed, get medical help or contact a Poison Control Center right away.

Directions

- flush the affected eye(s) as needed
- control the rate of flow of solution by placing pressure on the bottle

When using an eye cup

- rinse the cup with Eye Wash immediately before each use
- avoid contamination of the rim and inside surfaces of the cup
- fill the cup half full with Eye Wash and apply the cup to the affected eye(s), pressing tightly to prevent the escape of the liquid
- tilt the head backward. Open eyelids wide and rotate eyeball to ensure thorough bathing with the wash.
- rinse the cup with clean water after each use

Other information

- store at room temperature 15° - 25°C (59° - 77°F)
- keep tightly closed

Inactive ingredients

boric acid, sodium borate, sodium chloride, hydrochloric acid PRESERVATIVE ADDED: edetate disodium, polyhexamethylene biguanide

Question or comments?

call 1-800-616-2471

HOW SUPPLIED

Product: 50090-3159

NDC: 50090-3159-0 118 mL in a BOTTLE / 1 in a BOX